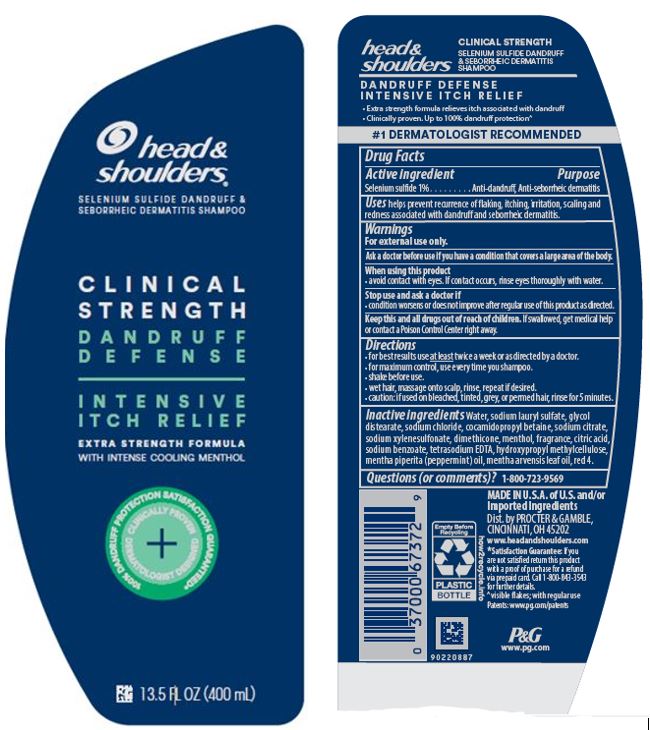 DRUG LABEL: Head and Shoulders Clinical Strength Dandruff Defense Intensive Itch Relief
NDC: 69423-526 | Form: LOTION/SHAMPOO
Manufacturer: The Procter & Gamble Manufacturing Company
Category: otc | Type: HUMAN OTC DRUG LABEL
Date: 20251231

ACTIVE INGREDIENTS: SELENIUM SULFIDE 1 g/100 mL
INACTIVE INGREDIENTS: COCAMIDOPROPYL BETAINE; EDETATE DISODIUM; MENTHOL, UNSPECIFIED FORM; HYPROMELLOSE, UNSPECIFIED; WATER; SODIUM LAURYL SULFATE; GLYCOL DISTEARATE; SODIUM CHLORIDE; SODIUM XYLENESULFONATE; DIMETHICONE; SODIUM BENZOATE; FD&C RED NO. 4; SODIUM CITRATE; CITRIC ACID MONOHYDRATE; PEPPERMINT OIL; MENTHA ARVENSIS LEAF OIL

Head and Shoulders®
Clinical Strength Dandruff Defense Intensive Itch Relief Shampoo

Drug Facts

Active ingredient

Selenium Sulfide 1%

Purpose

Anti-dandruff, anti-seborrheic dermatitis

Uses

helps prevent recurrence of flaking, itching, irritation, scaling and redness associated with dandruff and seborrheic dermatitis.

Warnings

For external use only.

Ask a doctor before use if you have a condition that covers a large area of the body.

WHEN USING

avoid contact with eyes. If contact occurs, rinse eyes thoroughly with water.

Stop use and ask a doctor if

condition worsens or does not improve after regular use of this product as directed

KEEP OUT OF REACH OF CHILDREN

Keep this and all drugs out of reach of children. If swallowed, get medical help or contact a Poison Control Center right away.

Directions

- for best results use at least twice a week or as directed by a doctor.
- for maximum dandruff control, use every time you shampoo.
- shake before use.
- wet hair, massage onto scalp, rinse, repeat if desired.
- caution: if used on bleached, tinted, grey, or permed hair, rinse for 5 minutes.

Inactive ingredients

Water, sodium lauryl sulfate, glycol distearate, sodium chloride, cocamidopropyl betaine, sodium citrate, sodium xylenesulfonate, dimethicone,menthol, fragrance, citric acid, sodium benzoate, tetrasodium EDTA, hydroxypropyl methylcellulose, mentha piperita (peppermint) oil,mentha arvensis leaf oil, red 4.

Questions (or comments)?

1-800-723-9569

Dist. by PROCTER & GAMBLE,
CINCINNATI, OH 45202

PRINCIPAL DISPLAY PANEL - BOTTLE LABEL

head &

shoulders ®
selenium sulfide dandruff &

seborrheic dermatitis shampoo

Clinical Strength

Dandruff Defense

Intensive

Itch Relief

13.5 FL OZ (400 mL)